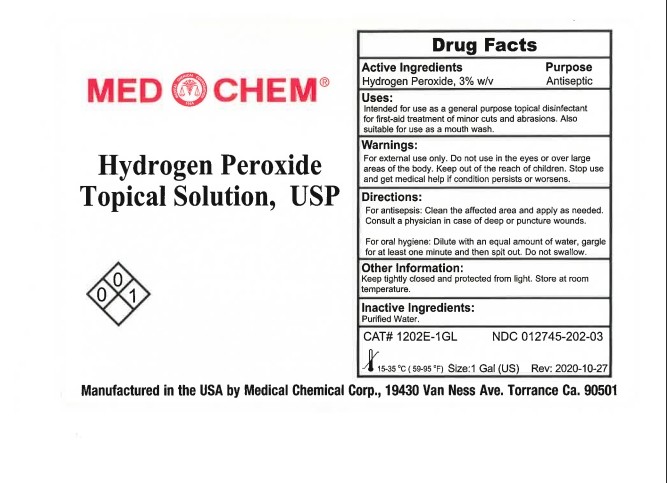 DRUG LABEL: HYDROGEN PEROXIDE
NDC: 12745-202 | Form: LIQUID
Manufacturer: Medical Chemical Corporation
Category: otc | Type: HUMAN OTC DRUG LABEL
Date: 20250903

ACTIVE INGREDIENTS: HYDROGEN PEROXIDE 8.57 g/100 mL
INACTIVE INGREDIENTS: WATER

Hydrogen Peroxide 3% Label

PURPOSE

Usage: Intended for use as a general purpose topical antiseptic for first-aid treatment of minor cuts and abrasions. In case of deep or puncture wounds consult a physician. Discontinue use and get medical attention if redness, irritation or infection develops.

Active ingredient: hydrogen peroxide, 3% w/v in water.

KEEP OUT OF REACH OF CHILDREN

For External Use Only. Do not use in eyes or over large areas of the body. Keep out of the reach of children.

INDICATIONS AND USAGE

Usage: Intended for use as a general purpose topical antiseptic for first-aid treatment of minor cuts and abrasions. In case of deep or puncture wounds consult a physician. Discontinue use and get medical attention if redness, irritation or infection develops.

WARNINGS

For External Use Only. Do not use in eyes or over large areas of the body. Keep out of the reach of children.

Dosage and administration section

For oral hygiene, dilute with an equal volume of water and gargle for about one minute. Rinse with water. In case of accidental ingestion contact a physician or a poison control center.

Active ingredient: hydrogen peroxide, 3% w/v in water.